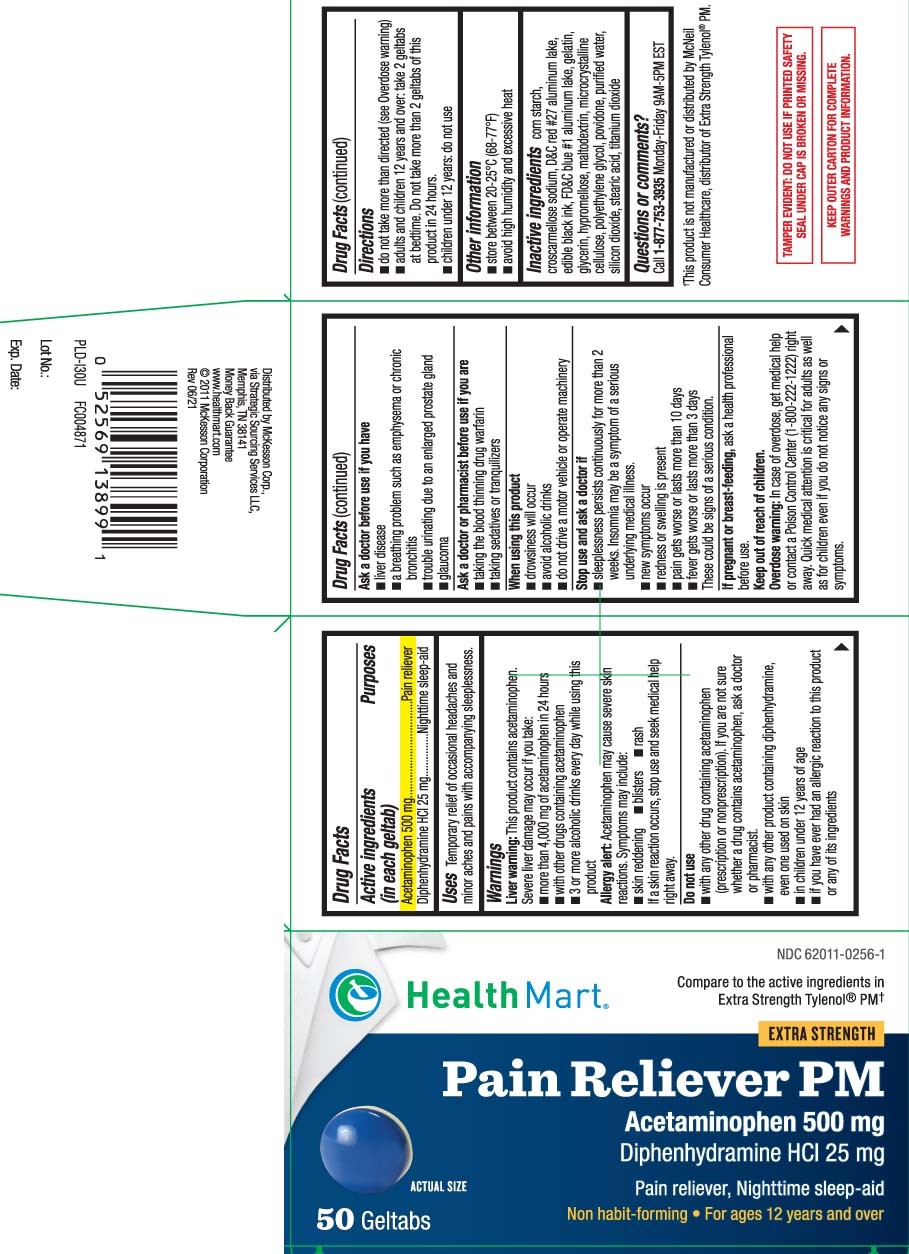 DRUG LABEL: Pain Reliever PM
NDC: 62011-0256 | Form: TABLET, COATED
Manufacturer: Strategic Sourcing Services LLC
Category: otc | Type: HUMAN OTC DRUG LABEL
Date: 20251008

ACTIVE INGREDIENTS: ACETAMINOPHEN 500 mg/1 1; DIPHENHYDRAMINE HYDROCHLORIDE 25 mg/1 1
INACTIVE INGREDIENTS: STARCH, CORN; D&C RED NO. 27; FD&C BLUE NO. 1; GELATIN; GLYCERIN; HYPROMELLOSES; MALTODEXTRIN; CELLULOSE, MICROCRYSTALLINE; POLYETHYLENE GLYCOL, UNSPECIFIED; POVIDONE; WATER; SILICON DIOXIDE; STEARIC ACID; TITANIUM DIOXIDE; CROSCARMELLOSE SODIUM; ALUMINUM OXIDE; SODIUM STARCH GLYCOLATE TYPE A CORN

Drug Facts

Active ingredients (in each geltab)

Acetaminophen 500 mg

Diphenhydramine HCl 25 mg

Purposes

Pain reliever

Nighttime sleep-aid

Uses

temporary relief of occasional headaches and minor aches and pains with accompanying sleeplessness

Warnings

Liver warning: This product contains acetaminophen. Severe liver damage may occur if you take:

- more than 4,000 mg of acetaminophen in 24 hours
- with other drugs containing acetaminophen
- 3 or more alcoholic drinks every day while using this product

Allergy alert: Acetaminophen may cause severe skin reactions. Symptoms may include:

- skin reddening
- blisters
- rash

If a skin reaction occurs, stop use and seek medical help right away.

Do not use

- with any other drug containing acetaminophen (prescription or nonprescription). If you are not sure whether a drug contains acetaminophen, ask a doctor or pharmacist.
- with any other product containing diphenhydramine, even one used on skin
- in children under 12 years of age
- if you have ever had an allergic reaction to this product or any of its ingredients

Ask a doctor before use if you have

- liver disease
- a breathing problem such as emphysema or chronic bronchitis
- trouble urinating due to an enlarged prostate gland
- glaucoma

Ask a doctor or pharmacist before use if you are

- taking the blood thinning drug warfarin
- taking sedatives or tranquilizers

When using this product

- drowsiness will occur
- avoid alcoholic drinks
- do not drive a motor vehicle or operate machinery

Stop use and ask a doctor if

- sleeplessness persists continuously for more than 2 weeks. Insomnia may be a symptom of a serious underlying medical illness.
- new symptoms occur
- redness or swelling is present
- pain gets worse or lasts more than 10 days
- fever gets worse or lasts more than 3 days

These could be signs of a serious condition.

If pregnant or breast-feeding,

ask a health professional before use.

Keep out of reach of children.

Overdose warning: In case of overdose, get medical help or contact a Poison Control Center (1-800-22201222) right away: Quick medical attention is critical for adults as well as for children even if you do not notice any signs or symptoms.

Directions

- do not take more than directed (see overdose warning)
- adults and children 12 years and over: take 2 geltabs at bedtime. Do not take more than 2 geltabs of this product in 24 hours.
- children under 12 years: do not use

Other information

- store at room temperature 20º-25ºC (68º-77ºF)
- avoid high humidity and excessive heat

Inactive ingredients

corn starch, croscarmellose sodium*, D&C red #27 aluminum lake, edible black ink, FD&C blue #1 aluminum lake, gelatin, glycerin, hypromellose, maltodextrin, microcrystalline cellulose, polyethylene glycol, povidone, purified water, silicon dioxide, sodium starch glycolate*, stearic acid, titanium dioxide

*contains one or more of these ingredients

Questions or comments?

Call 1-877-753-3935 Monday-Friday 9AM-5PM EST

Principal Display Panel

Compare to the active ingredients in Extra Strength TYLENOL PM®†

EXTRA STRENGTH

Pain Reliever PM

ACETAMINOPHEN 500 mg,

Diphenhydramine HCl 25 mg

Pain reliever/Nighttime sleep-aid

Non-habit forming • For ages 12 years and over

GELTABS

†This product is not manufactured or distributed by McNeil Consumer Healthcare, distributor of Extra Strength Tylenol® PM.

TAMPER EVIDENT: DO NOT USE IF PRINTED SAFETY SEAL UNDER CAP IS BROKEN OR MISSING.

KEEP OUTER CARTON FOR COMPLETE WARNINGS AND PRODUCT INFORMATION.

Distributed by McKesson

6555 State Highway 161 Irving, TX 75039

www.healthmart.com

Product Label

HEALTHMART Pain Reliever PM